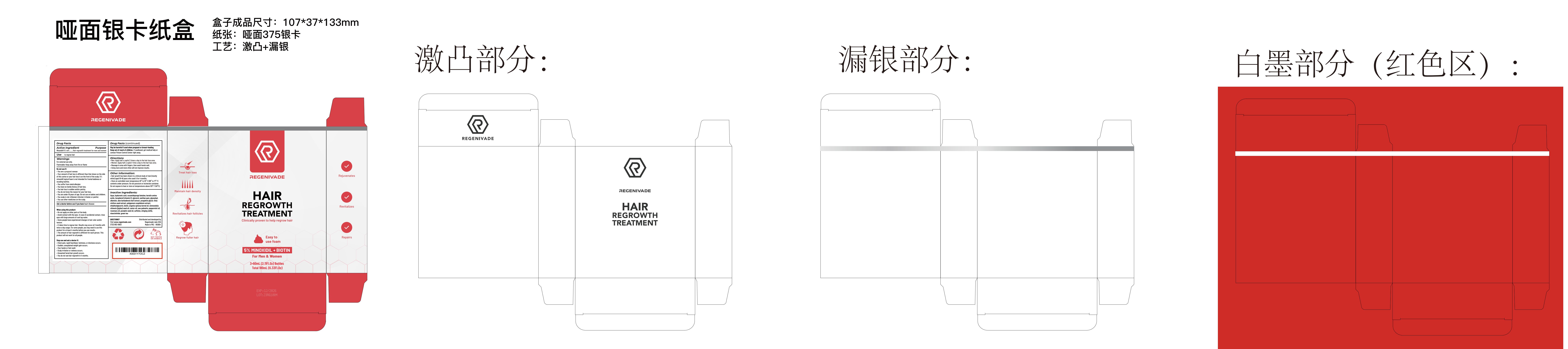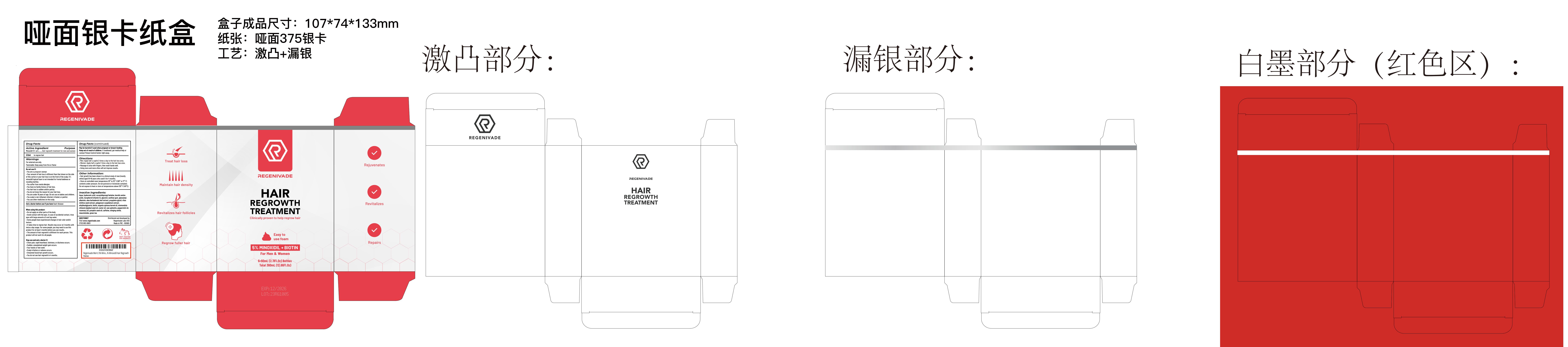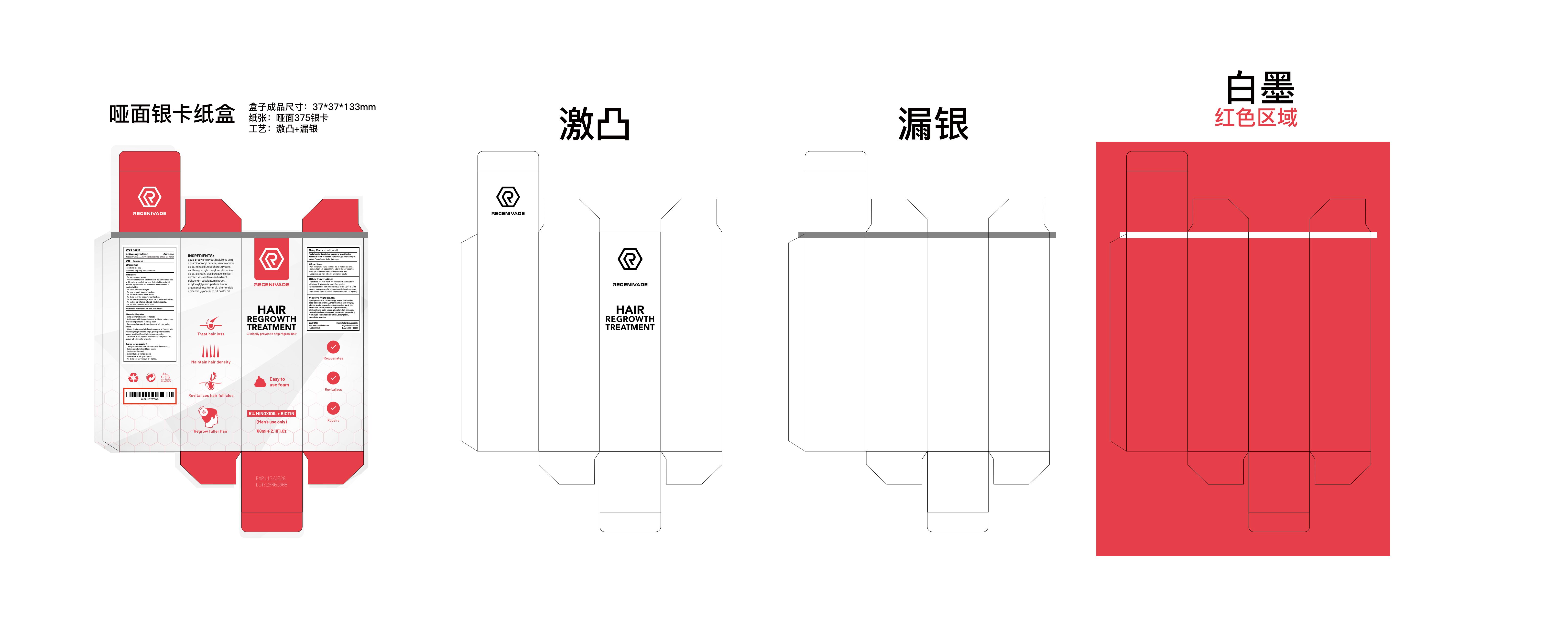 DRUG LABEL: Regenivade Hair Growth Foam
NDC: 81653-008 | Form: LIQUID
Manufacturer: Guangzhou Jianyuan Biological Technology.Co.,Ltd
Category: otc | Type: HUMAN OTC DRUG LABEL
Date: 20231128

ACTIVE INGREDIENTS: MINOXIDIL 5 g/100 mL
INACTIVE INGREDIENTS: VITIS VINIFERA POLLEN; WATER; SAW PALMETTO; ROSEMARY OIL; URTICA DIOICA; POLYGONUM CUSPIDATUM LEAF; PROPYLENE GLYCOL; BIOTIN; JOJOBA OIL; PEPPERMINT OIL; N-ETHYLHEXEDRONE; HYALURONIC ACID; GLYOXYLOYL CARBOCYSTEINE; ALLANTOIN; PUMPKIN SEED OIL; CAFFEINE; NIACIN; GREEN TEA LEAF; XANTHAN GUM; COCAMIDOPROPYL BETAINE; ARGAN OIL; CASTOR OIL; AMINO ACIDS, HAIR KERATIN; .ALPHA.-TOCOPHEROL; GLYCERIN; ALOE VERA LEAF

81653-008

Active Ingredient

Minoxidil 5% w/ v.

Purpose

Hair regrowth treatment for men and women

Use

To regrow hair

Warnings

For external use only.
Flammable: Keep away from fire or flame

Do not use if :

*You are a pregnant woman
*Your amount of hair loss is different than that shown on the side of this carton or your hair loss is on the front of the scalp.5% minoxidil topical foam is not intended for frontal baldness or
receding hairline.
.You suffer from metal allergies
.You have no family history of hair loss.
.You hair loss is sudden and/or patchy.
.You do not know the reason for your hair loss.
*You are under 18 years of age. Do not use on babies and children.
*You scalp is red, inflamed, infected, irritated, or painful.
·You use other medicines on the scalp.

When Using

●Do not apply on other parts of the body
●Avoid contact with the eyes. In case of accidental contact, rinse
eyes with large amounts of cool tap water.
●Some people have experienced changes in hair color and/or texture.
●It takes time to regrow hair. Results may occur at 2 months withtwice a day usage. For some people, you may need to use this product for at least 4 months before you see results.
●The amount of hair regrowth is different for each person. Thisproduct will not work for all people.

Stop Use

.Chest pain, rapid heartbeat, faintness, or dizziness occurs.
.Sudden, unexplained weight gain occurs.
.Your hands or feet swell.
. Scalp irritation or redness occurs.
.Unwanted facial hair growth occurs.
·You do not see hair regrowth in 4 months.

Ask Doctor

If have Allergy, plz check with doctor

Keep Oot Of Reach Of Children

Yes, Keep Oot Of Reach Of Children

Directions

●Men: Apply half a capful 2 times a day to the hair loss area.
●Women: Apply half a capful 1 time a day to the hair loss area.
●Massage to area with fingers, then wash hands well.
●Using more and more often will not improve results.

Other information

.Hair growth has been shown in a clinical study of men (mostly
white) aged 18-49 years who used it for 4 months.
·Store at controlled room temperature 20°to 25°C (68° to 77°F)
contents under pressure. Do not puncture or incinerate container.
Do not expose to heat or store at temperatures above 120°F (49℃).

Inactive ingredients

Aqua,hyaluronic acid, Cocamidopropyl betaine,keratin amino acids,tocopherol (vitamin E), glycerol, xanthan gum, Glyoxyloyl , allantoin, aloe barbadensis leaf extract, propylene glycol, vitas vinifera seed extract, polygonum cuspidatum extract, ethylhexlglycerin, biotin, argania spinosa kernel oil,simmondsia chinesis (jojoba) seed oil, castor oil, saw palmetto, peppermint oil,rosemary oil, pumpkin seed oil, caffeine, stinging nettle, niancinimide, Green tea.

Questions

Visit www.regenivade.com
(732) 893-0603